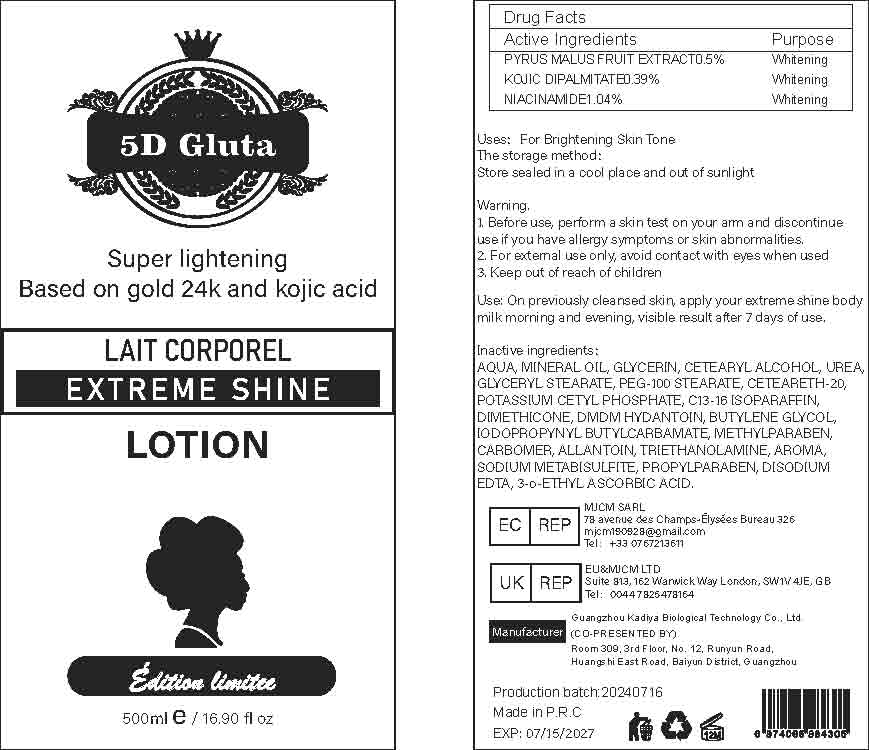 DRUG LABEL: Extreme Shine BodyLotion
NDC: 84423-026 | Form: EMULSION
Manufacturer: Guangzhou Kadiya Biotechnology Co., Ltd.
Category: otc | Type: HUMAN OTC DRUG LABEL
Date: 20240723

ACTIVE INGREDIENTS: NIACINAMIDE 5.2 mg/500 mL; APPLE 2.5 mg/500 mL; KOJIC DIPALMITATE 1.95 mg/500 mL
INACTIVE INGREDIENTS: EDETATE DISODIUM; DMDM HYDANTOIN; C13-16 ISOPARAFFIN; MINERAL OIL; TROLAMINE; CETOSTEARYL ALCOHOL; CARBOXYPOLYMETHYLENE; ALLANTOIN; UREA; PEG-100 STEARATE; DIMETHICONE; WATER; POTASSIUM CETYL PHOSPHATE; SODIUM METABISULFITE; PROPYLPARABEN; 3-O-ETHYL ASCORBIC ACID; GLYCERIN; GLYCERYL MONOSTEARATE; POLYOXYL 20 CETOSTEARYL ETHER; BUTYLENE GLYCOL; IODOPROPYNYL BUTYLCARBAMATE; METHYLPARABEN

Uses：
For Brightening Skin Tone

INACTIVE INGREDIENT

AQUA、MINERAL OIL、GLYCERIN、CETEARYL ALCOHOL、UREA、GLYCERYL STEARATE、PEG-100 STEARATE、CETEARETH-20、POTASSIUM CETYL PHOSPHATE、C13-16 ISOPARAFFIN、DIMETHICONE、DMDM HYDANTOIN、BUTYLENE GLYCOL、IODOPROPYNYL BUTYLCARBAMATE、METHYLPARABEN、CARBOMER、ALLANTOIN、TRIETHANOLAMINE、AROMA、SODIUM METABISULFITE、PROPYLPARABEN、DISODIUM EDTA、3-o-ETHYL ASCORBIC ACID

Warning.
1.Before use, perform a skin test on your arm and discontinue use if you have allergy symptoms or skin abnormalities.
2、For external use only, avoid contact with eyes when used
3、Keep out of reach of children

INDICATIONS AND USAGE

On provioushy cloansod skin. annly vour ovtrome shine bodmilk morning and evening, visible result after 7 days of use.

KEEP OUT OF REACH OF CHILDREN SECTION

Active Ingredients
PYRUS MALUS FRUIT EXTRACT 0.5%
KOJIC DIPALMITATE 0.39%
NIACINAMIDE 1.04%

DOSAGE AND ADMINISTRATION

On provioushy cloansod skin. annly vour ovtrome shine bodmilk morning and evening, visible result after 7 days of use.

Drug Facts
Active Ingredients
PYRUS MALUS FRUIT EXTRACT 0.5%
KOJIC DIPALMITATE 0.39%
NIACINAMIDE 1.04%
Uses：
For Brightening Skin Tone
The storage method：
Store sealed in a cool place and out of sunlight
Warning.
1.Before use, perform a skin test on your arm and discontinue use if you have allergy symptoms or skin abnormalities.
2、For external use only, avoid contact with eyes when used
3、Keep out of reach of children
Inactive ingredients：
AQUA、MINERAL OIL、GLYCERIN、CETEARYL ALCOHOL、UREA、GLYCERYL STEARATE、PEG-100 STEARATE、CETEARETH-20、POTASSIUM CETYL PHOSPHATE、C13-16 ISOPARAFFIN、DIMETHICONE、DMDM HYDANTOIN、BUTYLENE GLYCOL、IODOPROPYNYL BUTYLCARBAMATE、METHYLPARABEN、CARBOMER、ALLANTOIN、TRIETHANOLAMINE、AROMA、SODIUM METABISULFITE、PROPYLPARABEN、DISODIUM EDTA、3-o-ETHYL ASCORBIC ACID